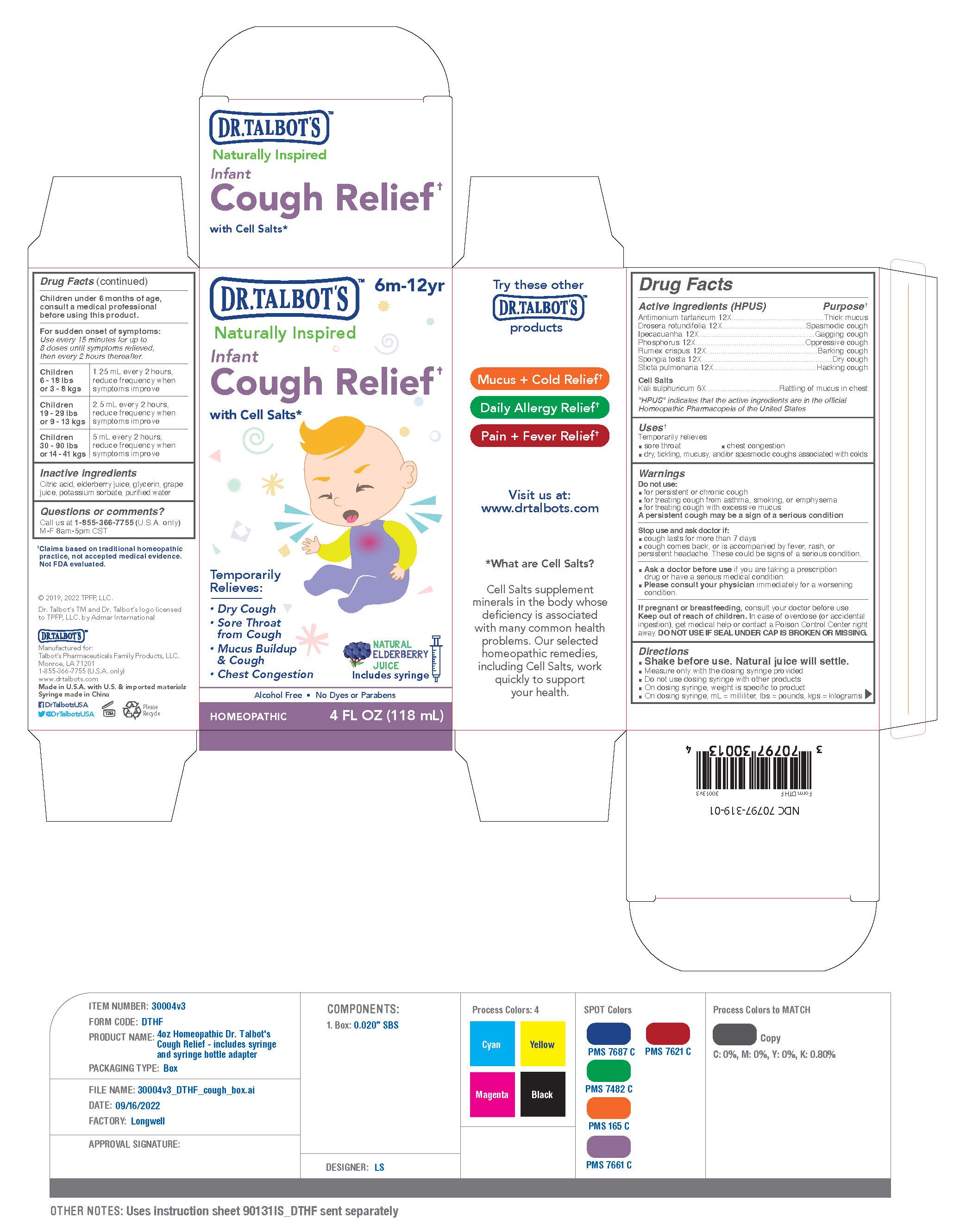 DRUG LABEL: Dr Talbots Infant Cough Relief
NDC: 70797-319 | Form: LIQUID
Manufacturer: Talbot’s Pharmaceuticals Family Products, LLC.
Category: homeopathic | Type: HUMAN OTC DRUG LABEL
Date: 20220912

ACTIVE INGREDIENTS: IPECAC 12 [hp_X]/118 mL; PULMONARIA OFFICINALIS WHOLE 12 [hp_X]/118 mL; PHOSPHORUS 12 [hp_X]/118 mL; ANTIMONY TARTRATE ION 12 [hp_X]/118 mL; SPONGIA OFFICINALIS SKELETON, ROASTED 12 [hp_X]/118 mL; RUMEX CRISPUS ROOT 12 [hp_X]/118 mL; DROSERA ROTUNDIFOLIA FLOWERING TOP 12 [hp_X]/118 mL
INACTIVE INGREDIENTS: GLYCERIN; WATER; EUROPEAN ELDERBERRY JUICE; CITRIC ACID MONOHYDRATE; POTASSIUM SORBATE; CONCORD GRAPE JUICE

ACTIVE INGREDIENTS

Active ingredients (HPUS)
Antimonium tartaricum 12X
Drosera rotundifolia 12X
Ipecacuanha 12X
Phosphorus 12X
Rumex crispus 12X
Spongia tosta 12X
Sticta pulmonaria 12X
Cell Salts
Kali sulphuricum 6X

Ask a doctor before use if you are taking a prescription drug or have a serious medical condition.
Please consult your physician immediately for a worsening condition .

PREGNANCY

Pregnant or breastfeeding

If pregnant or breastfeeding, consult your doctor before use.(SEE ATTCHED PRODUCT LABEL IMAGE)

KEEP OUT OF REACH OF CHILDREN SECTION

Keep out of reach of children

Keep out of reach of children. In case of overdoes (or accidental ingestion), get medical help or contact a Poison Control Center right away. DO NOT USE IF SEAL UNDER CAP IS BROKEN OR MISSING.(SEE ATTCHED PRODUCT LABEL IMAGE)

INACTIVE INGREDIENTS

Inactive ingredients (SEE PRODUCT LABEL IMAGE)
Citric acid, elderberry juice, glycerin, grape
juice, potassium sorbate, purified water

DOSAGE

Children under 6 months of age, consult a medical professional before using this product.(SEE ATTCHED PRODUCT IMAGE)

For sudden onset of symptoms: Use every 15 minutes for up to 8 doses until symptoms relieved, then every 2 hours thereafter.

Children 6 - 18 lbs or 3 - 8 kgs

1.25 ml every 2 hours, reduce frequency when symptoms improve

Children 19 - 29 lbs or 9 - 13 kgs

2.5 ml every 2 hours, reduce frequency when symptoms improve

Children 30 - 90 lbs or 14 - 41 kgs

5 ml every 2 hours, reduce frequency when symptoms improve

QUESTION

Questions

Questions or Comments?(SEE ATTCHED PRODUCT LABEL IMAGE)

INSTRUCTIONS

For sudden onset of symptoms: (SEE ATTCHED PRODUCT LABEL IMAGE)
Use every 15 minutes for up to
8 doses until symptoms relieved,
then every 2 hours thereafter.

Children
6 - 18 lbs
or 3 - 8 kgs

1.25 mL every 2 hours,
reduce frequency when
symptoms improve

Children
19 - 29 lbs
or 9 - 13 kgs

2.5 mL every 2 hours,
reduce frequency when
symptoms improve

Children
30 - 90 lbs
or 14 - 41 kgs

5 mL every 2 hours,
reduce frequency when
symptoms improve

Warnings

Do not use:

- for persistent or chronic cough
- for treating cough from asthama, smoking, or emphysema
- for treating cough with excessive mucus

A persistent cough may be a sign of a serious condition

Purpose

Temporarily Relieves:

- Dry Cough
- Sore Throat from cough
- Mucus Buildup & Cough
- Chest Congestion

Usage

Uses

Temporarily relieves

- sore throat
- chest congestion
- dry, ticking, mucusy, and/or spasmodic coughs associated with colds

PRINCIPAL DISPLAY

Principal Display Panel